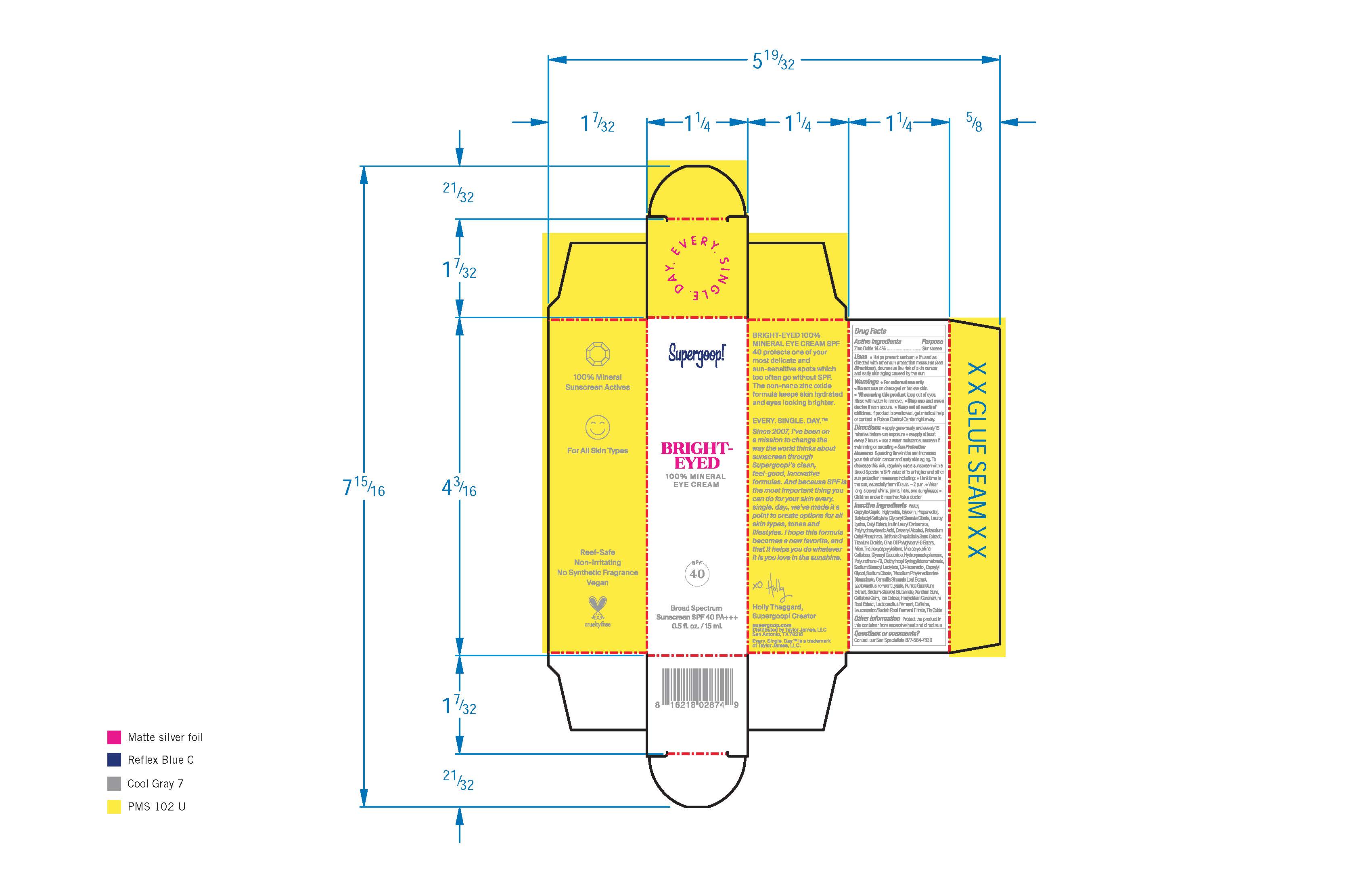 DRUG LABEL: Bright-eyed 100% mineral Eye Cream Broad Spectrum Sunscreen SPF 40
NDC: 75936-149 | Form: CREAM
Manufacturer: Supergoop, LLC
Category: otc | Type: HUMAN OTC DRUG LABEL
Date: 20241204

ACTIVE INGREDIENTS: ZINC OXIDE 14.4 g/100 mL
INACTIVE INGREDIENTS: LACTOBACILLUS REUTERI; CAFFEINE; GLYCERYL STEARATE CITRATE; LAUROYL LYSINE; PUNICA GRANATUM ROOT BARK; CETOSTEARYL ALCOHOL; MICA; TRIETHOXYCAPRYLYLSILANE; SODIUM CITRATE, UNSPECIFIED FORM; SODIUM STEAROYL GLUTAMATE; MEDIUM-CHAIN TRIGLYCERIDES; PROPANEDIOL; BUTYLOCTYL SALICYLATE; CETYL ESTERS WAX; CARBOXYMETHYLCELLULOSE SODIUM, UNSPECIFIED FORM; STANNIC OXIDE; HEDYCHIUM CORONARIUM ROOT; WATER; GLYCERIN; CAPRYLYL GLYCOL; TRISODIUM ETHYLENEDIAMINE DISUCCINATE; GREEN TEA LEAF; XANTHAN GUM; LEUCONOSTOC/RADISH ROOT FERMENT FILTRATE; FERRIC OXIDE RED; POTASSIUM CETYL PHOSPHATE; GRIFFONIA SIMPLICIFOLIA SEED; MICROCRYSTALLINE CELLULOSE; HYDROXYACETOPHENONE; SODIUM STEAROYL LACTYLATE; 1,2-HEXANEDIOL; DIETHYLHEXYL SYRINGYLIDENEMALONATE; POLYHYDROXYSTEARIC ACID (2300 MW); TITANIUM DIOXIDE

Bright-eyed 100% mineral Eye Cream Broad Spectrum Sunscreen SPF 40

Active Ingredients Purpose

Zinc Oxide 14.4 % Sunscreen

Uses

Helps prevent Sunburn

If used as directed with other sun protection measures (see Directions), decreases the risk of skin cancer and early skin aging caused by the sun

Keep out of reach of children. If product is swallowed, get medical help or contact a Poison Control Center right away.

Stop use and ask a doctor if rash occurs

Warnings

For external use only

Do not use on damaged or broken skin
When using this product keep out of eyes. Rinse with water to remove

INACTIVE INGREDIENT

Inactive Ingredients Water, Caprylic/Capric Triglyceride, Glycerin, Propanediol, Butyloctyl Salicylate, Glyceryl Stearate Citrate, Lauroyl Lysine, Cetyl Esters, Inulin Lauryl CarbamatePolyhydroxystearic Acid, Cetearyl Alcohol, Potassium Cetyl phosophate, Griffonia Simplicifolia Seed Extract, Titanium Dioxide, Olive Oil Polyglyceryl-6 Esters, Mica, Triethoxycaprylylsilane, Microcrystalline cellulose, Glyceryl Glucoside, Hydroxyacetophenone, Polyurethane-79, Diethylhexyl Syringylidenemalonate, Sodium Stearoyl Lactylate, 1,2-Hexanediol, Caprylyl Glycol, Sodium Citrate, Trisodium Ethylenediamine Disuccinate, Camellia Sinensis Leaf Extract, Lactobacillus Ferment Lysate, Punica Granatum Extract, Sodium Citrate, Sodium Stearoyl Glutamate, Xanthan Gum, Cellulose Gum, Iron Oxides, Hedychium Coronarium Root Extract, Lactobacillus Ferment, Caffeine, Leuconostoc/Radish Root Ferment Filtrate, Tin Oxide.

Directions

• Apply generously and evenly as the last step in your skincare routine, before makeup and 15 minutes before sun exposure. • Reapply at least every 2 hours. • Use a water resistant sunscreen if swimming or sweating. • Children under 6 months of age: ask a doctor. • Sun Protection Measures. Spending time in the sun increases your risk of skin cancer and early skin aging. To decrease this risk, regularly use a sunscreen with a Broad Spectrum SPF value of 15 or higher and other sun protection measures including: • limit time in the sun, especially from 10 a.m.-2 p.m. • wear long-sleeved shirts, pants, hats, and sunglasses.

PACKAGE LABEL

Supergoop!

Bright-eyed

100% Mineral Eye Cream

SPF 40

Broad Spectrum

Sunscreen SPF 40 PA +++

0.5 fl. oz. / 15 mL